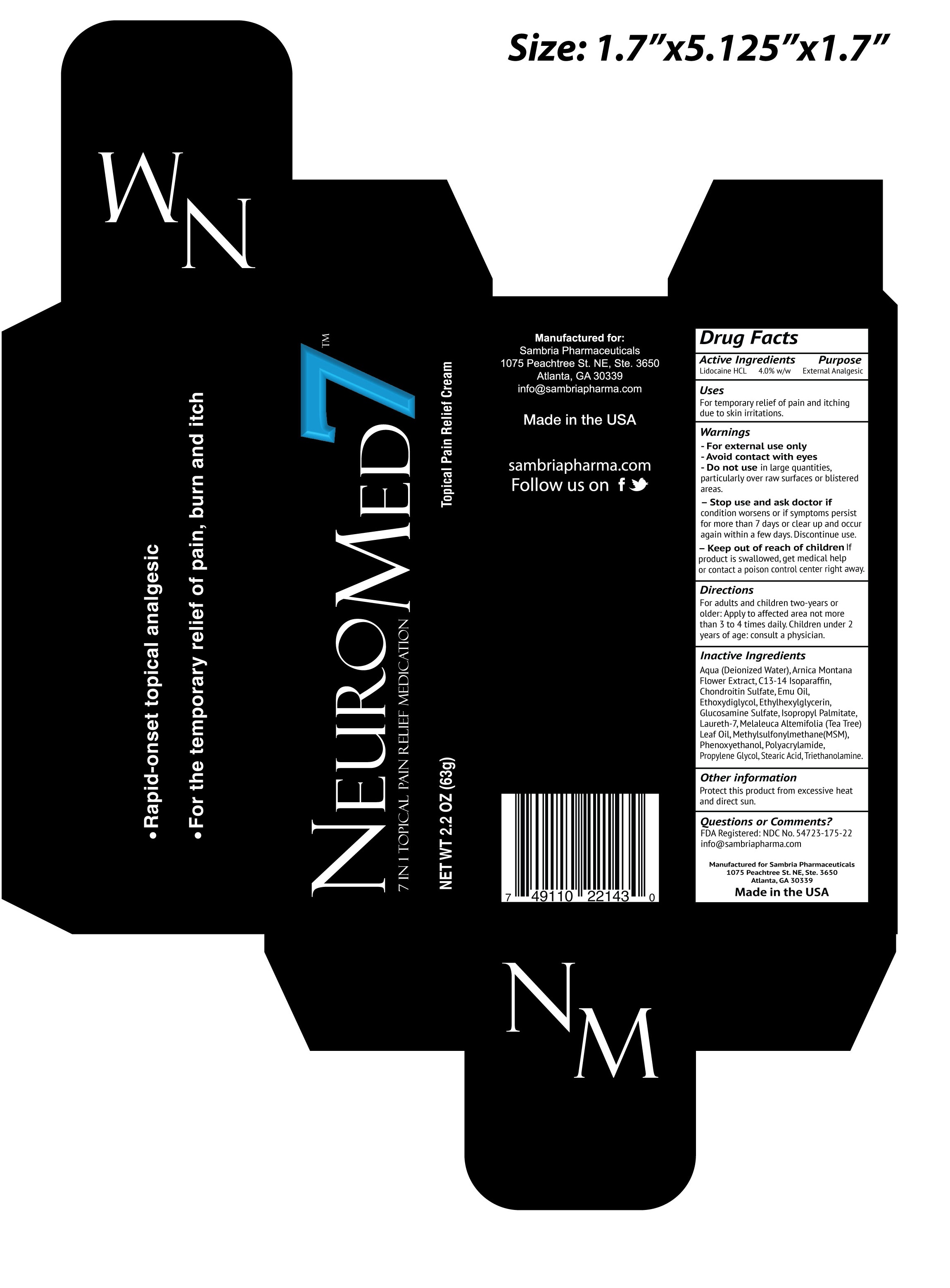 DRUG LABEL: NeuroMed 7 Topical Pain Relief
NDC: 54723-175 | Form: CREAM
Manufacturer: Sambria Pharmaceuticals, LLC
Category: otc | Type: HUMAN OTC DRUG LABEL
Date: 20251112

ACTIVE INGREDIENTS: LIDOCAINE HYDROCHLORIDE 4 g/100 g
INACTIVE INGREDIENTS: ARNICA MONTANA FLOWER; WATER; C13-14 ISOPARAFFIN; SODIUM CHONDROITIN SULFATE (PORCINE; 5500 MW); EMU OIL; DIETHYLENE GLYCOL MONOETHYL ETHER; ETHYLHEXYLGLYCERIN; GLUCOSAMINE SULFATE; ISOPROPYL PALMITATE; MELALEUCA ALTERNIFOLIA LEAF; DIMETHYL SULFONE; PHENOXYETHANOL; PROPYLENE GLYCOL; STEARIC ACID; TROLAMINE

NeuroMed 7 Topical Pain Relief Cream

Active Ingredients

Lidocaine HCL 4.0% w/w

Purpose

External Anesthetic

Uses

For temporary relief of pain and itching due to minor skin irritations.

Warnings

- For external use only.

- Avoid contact with eyes.

DO NOT USE

- Do not usein large quantities, particularly over raw surfaces or blistered areas.

- Stop use and ask a doctorif condition worsens, or if symptoms persist for more than 7 days or clear up and occur again within a few days. Discontinue use.

- Keep out of reach of children. If product is swallowed, get medical help or contact a Poison Control Center right away.

Directions

For adults and children two-years or older: Apply to affected area not more than 3 or 4 times daily. Children under 2 years of age: consult a physician.

Inactive Ingredients

Aqua (Deionized Water), Arnica Montana Floweri Extract, C13-14 Isoparaffin, Chondroitin Sulfate, Emu Oil, Ethoxydiglycol, Ethylhexylglycerin, Glucosamine Sulfate, Isopropyl Palmitate, Laureth-7, Melaleuca Alternifolia (Tea Tree) Oil, Methylsulfonylmenthane (MSM), Phenoxyethanol, Polyacrylamide, Propylene Glycol, Stearic Acid, Triethanolamine.

Other Information

Protect this product from excessive heat and direct sun.

Questions or Comments?

FDA Registered: NDC No 54723-175-22

info@sambriapharma.com